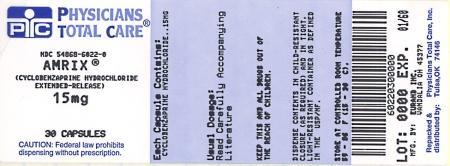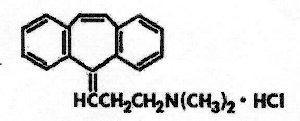 DRUG LABEL: AMRIX
NDC: 54868-6022 | Form: CAPSULE, EXTENDED RELEASE
Manufacturer: Physicians Total Care, Inc.
Category: prescription | Type: HUMAN PRESCRIPTION DRUG LABEL
Date: 20120806

ACTIVE INGREDIENTS: cyclobenzaprine hydrochloride 15 mg/1 1
INACTIVE INGREDIENTS: DIETHYL PHTHALATE; ETHYLCELLULOSE (10 MPA.S); GELATIN; SUCROSE; TITANIUM DIOXIDE; D&C YELLOW NO. 10; FD&C GREEN NO. 3; FD&C RED NO. 40; STARCH, CORN

AMRIX®
(Cyclobenzaprine Hydrochloride Extended-Release Capsules)

DESCRIPTION

AMRIX® (Cyclobenzaprine Hydrochloride Extended-Release Capsules) is a skeletal muscle relaxant which relieves muscle spasm of local origin without interfering with muscle function. The active ingredient in AMRIX extended-release capsules is cyclobenzaprine hydrochloride, USP. Cyclobenzaprine hydrochloride (HCl) is a white, crystalline tricyclic amine salt with the empirical formula C20H21N•HCl and a molecular weight of 311.9. It has a melting point of 217°C, and a pKa of 8.47 at 25°C. It is freely soluble in water and alcohol, sparingly soluble in isopropanol, and insoluble in hydrocarbon solvents. If aqueous solutions are made alkaline, the free base separates. Cyclobenzaprine HCl is designated chemically as 3-(5H-dibenzo[a,d] cyclohepten-5-ylidene)-N,N-dimethyl-1-propanamine hydrochloride, and has the following structural formula:

AMRIX extended-release capsules for oral administration are supplied in 15 and 30 mg strengths. AMRIX capsules contain the following inactive ingredients: diethyl phthalate NF, ethylcellulose NF (Ethocel Standard 10 Premium), gelatin, Opadry® Clear YS-1-7006, sugar spheres NF (20-25 mesh), and titanium dioxide. AMRIX 15 mg capsules also contain D&C yellow #10, FD&C green #3, and FD&C red #40. AMRIX 30 mg capsules also contain FD&C blue #1, FD&C blue #2, FD&C red #40, and FD&C yellow #6.

CLINICAL PHARMACOLOGY

Cyclobenzaprine relieves skeletal muscle spasm of local origin without interfering with muscle function. Cyclobenzaprine has not been shown to be effective in muscle spasm due to central nervous system disease. In animal models, cyclobenzaprine reduced or abolished skeletal muscle hyperactivity. Animal studies indicate that cyclobenzaprine does not act at the neuromuscular junction or directly on skeletal muscle. Such studies show that cyclobenzaprine acts primarily within the central nervous system at the brain stem as opposed to the spinal cord level, although an overlapping action on the latter may contribute to its overall skeletal muscle relaxant activity. Evidence suggests that the net effect of cyclobenzaprine is a reduction of tonic somatic motor activity, influencing both gamma (γ) and alpha (α) motor systems. Pharmacological studies in animals demonstrated a similarity between the effects of cyclobenzaprine and the structurally related tricyclic antidepressants, including reserpine antagonism, norepinephrine potentiation, potent peripheral and central anticholinergic effects, and sedation. Cyclobenzaprine caused slight to moderate increase in heart rate in animals.

Pharmacokinetics

Absorption

In a single-dose study comprised of healthy adult males (n=15), the dose adjusted ratios of the arithmetic means of AUC0-168 and AUC0-∞ indicated that exposure of the AMRIX 30 mg was about 16% and 10% higher than that of AMRIX 15 mg, respectively. The dose-adjusted ratios of the arithmetic means of Cmax indicated that the peak plasma concentration of AMRIX 30 mg was about 20% higher than that of AMRIX 15 mg. The half-lives and time to peak plasma cyclobenzaprine concentration were similar for both AMRIX 15 mg and 30 mg. These data are summarized below.

Table 1: Summary of Pharmacokinetic Parameters in Healthy Adult Subjects
Parameter Mean ± SD | AMRIX 15 mg (N=15) | AMRIX 30 mg (N=14)
AUC0-168 (ng•hr/mL) | 318.3 ± 114.7 | 736.6 ± 259.4
AUC0-∞ (ng•hr/mL) | 354.1 ± 119.8 | 779.9 ± 277.6
Cmax (ng/mL) | 8.3 ± 2.2 | 19.9 ± 5.9
Tmax (hrs) | 8.1 ± 2.9 | 7.1 ± 1.6
t1/2 (hrs) | 33.4 ± 10.3 | 32.0 ± 10.1
SD = standard deviation

A food effect study conducted in healthy adult subjects (n=15) utilizing a single dose of AMRIX 30 mg demonstrated a statistically significant increase in bioavailability when AMRIX 30 mg was given with food relative to the fasted state. There was a 35% increase in peak plasma cyclobenzaprine concentration (Cmax) and a 20% increase in exposure (AUC0-168 and AUC0-∞) in the presence of food. No effect, however, was noted in Tlag, Tmax, or the shape of the mean plasma cyclobenzaprine concentration versus time profile. Cyclobenzaprine in plasma was first detectable in both the fed and fasted states at 1.5 hours.

In a multiple-dose study utilizing AMRIX 30 mg administered once daily for 7 days in a group of healthy adult volunteers (n=35) a 2.5-fold accumulation of plasma cyclobenzaprine levels was noted at steady-state.

Metabolism and Elimination

Cyclobenzaprine is extensively metabolized and is excreted primarily as glucuronides via the kidney. Cytochromes P-450 3A4, 1A2, and, to a lesser extent, 2D6, mediate N-demethylation, one of the oxidative pathways for cyclobenzaprine. Cyclobenzaprine has an elimination half-life of 32 hours (range 8-37 hours; n=18); plasma clearance is 0.7 L/min following single dose administration of AMRIX.

Special Populations

Elderly

Although there were no notable differences in Cmax or Tmax, cyclobenzaprine plasma AUC is increased by 40% and the plasma half-life of cyclobenzaprine is prolonged in elderly subjects greater than 65 years of age (50 hours) after dosing with AMRIX compared to younger subjects (32 hours). Pharmacokinetic characteristics of cyclobenzaprine following multiple-dose administration of AMRIX in the elderly were not evaluated.

Table 2: Summary of Pharmacokinetic Parameters of AMRIX 30 mg Extended-Release Capsules, By Age Group
Parameter Mean ± SD | AMRIX 30 mg QD
Parameter Mean ± SD | 18 to 45 years (N=18) | 65 to 75 years (N=17)
AUC0-168 (ng•hr/mL) | 715.1 ± 264.2 | 945.9 ± 255.2
AUC0-∞ (ng•hr/mL) | 751.2 ± 271.5 | 1055.2 ± 301.9
Cmax (ng/mL)* | 19.2 ± 5.6 | 19.2 ± 5.1
Tmax (hrs)* | 6.8 ± 1.9 | 8.5 ± 2.3
t1/2 (hrs) | 32.4 ± 8.1 | 49.0 ± 8.3
* Measured over the entire 24 hour period
SD = standard deviation

Hepatic Impairment

In a pharmacokinetic study of immediate-release cyclobenzaprine in 16 subjects with hepatic impairment (15 mild, 1 moderate per Child-Pugh score), both AUC and Cmax were approximately double the values seen in the healthy control group. The pharmacokinetics of cyclobenzaprine in subjects with severe hepatic impairment is not known.

CLINICAL STUDIES

Efficacy was assessed in two double-blind, parallel-group, placebo-controlled studies of identical design of AMRIX 15 mg and 30 mg taken once daily in patients with muscle spasms associated with acute painful musculoskeletal conditions.

There were significant differences in the primary efficacy analysis, the patient’s rating of medication helpfulness, between the AMRIX 15 mg group and the placebo group at Days 4 and 14 in one study and between the AMRIX 30 mg group and the placebo group at Day 4 in the second study.

Table 3: Subject’s Rating of Medication Helpfulness - Study 1105
 | Day 4 |  | Day 14
 | Number of Subjects (%) |  | Number of Subjects (%)
 | Placebo (N = 64) | AMRIX 30 mg (N = 64) | Placebo (N = 64) | AMRIX 30 mg (N = 64)
Excellent | 1 (1.6%) | 3 (4.7%) | 12 (18.8%) | 15 (23.4%)
Very Good | 5 (7.8%) | 13 (20.3%) | 9 (14.1%) | 19 (29.7%)
Good | 15 (23.4%) | 22 (34.4%) | 10 (15.6%) | 15 (23.4%)
Fair | 24 (37.5%) | 20 (31.3%) | 16 (25.0%) | 10 (15.6%)
Poor | 10 (15.6%) | 5 (7.8%) | 9 (14.1%) | 4 (6.3%)
Missing | 9 (14.1%) | 1 (1.6%) | 8 (12.5%) | 1 (1.6%)

Table 4: Subject's Rating of Medication Helpfulness - Study 1106
 | Day 4 |  | Day 14
 | Number of Subjects (%) |  | Number of Subjects (%)
 | Placebo (N = 64) | AMRIX 15 mg (N = 63) | Placebo (N = 64) | AMRIX 15 mg (N = 63)
Excellent | 1 (1.6%) | 2 (3.2%) | 10 (15.6%) | 13 (20.6%)
Very Good | 10 (15.6%) | 12 (19.0%) | 12 (18.8%) | 21 (33.3%)
Good | 14 (21.9%) | 21 (33.3%) | 13 (20.3%) | 9 (14.3%)
Fair | 16 (25.0%) | 17 (27.0%) | 14 (21.9%) | 10 (15.9%)
Poor | 19 (29.7%) | 6 (9.5%) | 12 (18.8%) | 5 (7.9%)
Missing | 4 (6.3%) | 5 (17.9%) | 3 (4.7%) | 5 (7.9%)

In addition, one of the two studies demonstrated significant differences between the AMRIX 30 mg group and the placebo group in terms of patient-rated relief from local pain due to muscle spasm at Day 4 and Day 8, in subject-rated restriction of movement at Day 4 and Day 8, and in patient-rated global impression of change at Day 4, Day 8, and Day 14.

There were no significant treatment differences between the AMRIX treatment groups and the placebo group in physician's global assessment, in subject-rated restriction in activities of daily living, or quality of night-time sleep.

INDICATIONS AND USAGE

AMRIX is indicated as an adjunct to rest and physical therapy for relief of muscle spasm associated with acute, painful musculoskeletal conditions. Improvement is manifested by relief of muscle spasm and its associated signs and symptoms, namely, pain, tenderness, and limitation of motion.

AMRIX should be used only for short periods (up to two or three weeks) because adequate evidence of effectiveness for more prolonged use is not available and because muscle spasm associated with acute, painful musculoskeletal conditions is generally of short duration and specific therapy for longer periods is seldom warranted.

AMRIX has not been found effective in the treatment of spasticity associated with cerebral or spinal cord disease or in children with cerebral palsy.

CONTRAINDICATIONS

- Hypersensitivity to any component of this product.
- Concomitant use of monoamine oxidase (MAO) inhibitors or within 14 days after their discontinuation.
- Hyperpyretic crisis seizures and deaths have occurred in patients receiving cyclobenzaprine (or structurally similar tricyclic antidepressants) concomitantly with MAO inhibitor drugs.
- During the acute recovery phase of myocardial infarction, and in patients with arrhythmias, heart block conduction disturbances, or congestive heart failure.
- Hyperthyroidism.

WARNINGS

AMRIX is closely related to the tricyclic antidepressants, e.g., amitriptyline and imipramine. In short term studies for indications other than muscle spasm associated with acute musculoskeletal conditions, and usually at doses somewhat greater than those recommended for skeletal muscle spasm, some of the more serious central nervous system reactions noted with the tricyclic antidepressants have occurred (see WARNINGS, below, and ADVERSE REACTIONS).

Tricyclic antidepressants have been reported to produce arrhythmias, sinus tachycardia, prolongation of the conduction time leading to myocardial infarction and stroke. AMRIX may enhance the effects of alcohol, barbiturates, and other CNS depressants.

As a result of a two-fold higher cyclobenzaprine plasma levels in subjects with mild hepatic impairment, as compared to healthy subjects, following administration of immediate-release cyclobenzaprine and because there is limited dosing flexibility with AMRIX, use of AMRIX is not recommended in subjects with mild, moderate or severe hepatic impairment.

As a result of a 40% increase in cyclobenzaprine plasma levels and a 56% increase in plasma half-life following administration of AMRIX in elderly subjects as compared to young adults, use of AMRIX is not recommended in elderly.

PRECAUTIONS

General

Because of its atropine-like action, AMRIX should be used with caution in patients with a history of urinary retention, angle-closure glaucoma, increased intraocular pressure, and in patients taking anticholinergic medication.

Information for Patients

AMRIX, especially when used with alcohol or other CNS depressants, may impair mental and/or physical abilities required for performance of hazardous tasks, such as operating machinery or driving a motor vehicle.

Drug Interactions

AMRIX may have life-threatening interactions with MAO inhibitors. (See CONTRAINDICATIONS.) AMRIX may enhance the effects of alcohol, barbiturates, and other CNS depressants. Tricyclic antidepressants may block the antihypertensive action of guanethidine and similarly acting compounds. Tricyclic antidepressants may enhance the seizure risk in patients taking tramadol (ULTRAM® [tramadol HCl tablets, Ortho-McNeil Pharmaceutical] or ULTRACET® [tramadol HCl and acetaminophen tablets, Ortho-McNeil Pharmaceutical]).

Carcinogenesis, Mutagenesis, Impairment of Fertility

In rats treated with cyclobenzaprine for up to 67 weeks at doses of approximately 5 to 40 times the maximum recommended human dose, pale, sometimes enlarged, livers were noted and there was a dose-related hepatocyte vacuolation with lipidosis. In the higher dose groups, this microscopic change was seen after 26 weeks and even earlier in rats that died prior to 26 weeks; at lower doses, the change was not seen until after 26 weeks. Cyclobenzaprine did not affect the onset, incidence, or distribution of neoplasia in an 81-week study in the mouse or in a 105-week study in the rat. At oral doses of up to 10 times the human dose, cyclobenzaprine did not adversely affect the reproductive performance or fertility of male or female rats. Cyclobenzaprine did not demonstrate mutagenic activity in the male mouse at dose levels of up to 20 times the human dose.

A battery of mutagenicity tests using bacterial and mammalian systems for point mutations and cytogenic effects have provided no evidence for a mutagenic potential for cyclobenzaprine. An in vivo mouse bone micronucleus assay, an assessment of chromosomal aberrations (Chinese hamster ovary), and a mammalian microsome reverse mutation assay were negative.

Pregnancy

Pregnancy Category B: Reproduction studies have been performed in rats, mice, and rabbits at doses up to 20 times the human dose and have revealed no evidence of impaired fertility or harm to the fetus due to cyclobenzaprine. There are, however, no adequate and well-controlled studies in pregnant women. Because animal reproduction studies are not always predictive of human response, this drug should be used during pregnancy only if clearly needed.

Nursing Mothers

It is not known whether this drug is excreted in human milk. Because cyclobenzaprine is closely related to the tricyclic antidepressants, some of which are known to be excreted in human milk, caution should be exercised when AMRIX is administered to a nursing woman.

Pediatric Use

Safety and effectiveness of AMRIX has not been studied in pediatric patients.

Use in the Elderly

The plasma concentration and half-life of cyclobenzaprine are substantially increased in the elderly when compared to the general patient population (see CLINICAL PHARMACOLOGY, Pharmacokinetics, Special Populations, Elderly). Accordingly, AMRIX should not be used in the elderly.

ADVERSE REACTIONS

The most common adverse reactions in the two 14-day clinical efficacy trials and in the 7-day repeat-dose pharmacokinetic study are presented in Tables 5 and 6, respectively.

Table 5: Incidence of the Most Common Adverse Reactions Occurring in ≥ 3% of Subjects in Any Treatment Group in the Two Phase 3, Double-Blind AMRIX Trials
 | AMRIX 15 mg N=127 | AMRIX 30 mg N=126 | Placebo N=128
Dry mouth | 6% | 14% | 2%
Dizziness | 3% | 6% | 2%
Fatigue | 3% | 3% | 2%
Constipation | 1% | 3% | 0%
Somnolence | 1% | 2% | 0%
Nausea | 3% | 3% | 1%
Dyspepsia | 0% | 4% | 1%

Table 6: Incidence of the Most Common Adverse Reactions Occurring in ≥ 3% of Subjects in Any Treatment Group in the Seven-Day Pharmacokinetic Study of AMRIX
 | AMRIX 30 mg N = 36
Somnolence | 100%
Dry mouth | 58%
Headache NOS | 17%
Dizziness | 19%
Vision blurred | 3%
Nausea | 8%
Dysgeusia | 6%
Palpitations | 6%
Tremor | 6%
Dry throat | 8%
Acne NOS | 6%
Disturbance in attention | 6%
Insomnia | 0

In a postmarketing surveillance program (7607 patients treated with cyclobenzaprine 10 mg TID), the adverse reactions reported most frequently were drowsiness, dry mouth, and dizziness. The incidence of these common adverse reactions was lower in the surveillance program than in the controlled clinical studies:

Table 7: Most Common Adverse Reactions from Postmarketing Surveillance Program
 | Clinical Studies cyclobenzaprine 10 mg TID | Surveillance Program cyclobenzaprine 10 mg TID
Drowsiness | 39% | 16%
Dry mouth | 27% | 7%
Dizziness | 11% | 3%

Among the less frequent adverse reactions, there was no appreciable difference in incidence in controlled clinical studies or in the surveillance program. Adverse reactions which were reported in 1% to 3% of the patients were: fatigue/tiredness, asthenia, nausea, constipation, dyspepsia, unpleasant taste, blurred vision, headache, nervousness, and confusion. The following adverse reactions have been reported in post-marketing experience or with an incidence of less than 1% of patients in clinical trials with the 10 mg TID tablet:

Body as a Whole: Syncope; malaise.
Cardiovascular: Tachycardia; arrhythmia; vasodilatation; palpitation; hypotension.
Digestive: Vomiting; anorexia; diarrhea; gastrointestinal pain; gastritis; thirst; flatulence; edema of the tongue; abnormal liver function and rare reports of hepatitis, jaundice, and cholestasis.
Hypersensitivity: Anaphylaxis; angioedema; pruritus; facial edema; urticaria; rash.
Musculoskeletal: Local weakness.
Nervous System and Psychiatric: Seizures, ataxia; vertigo; dysarthria; tremors; hypertonia; convulsions; muscle twitching; disorientation; insomnia; depressed mood; abnormal sensations; anxiety; agitation; psychosis, abnormal thinking and dreaming; hallucinations; excitement; paresthesia; diplopia.
Skin: Sweating.
Special Senses: Ageusia; tinnitus.
Urogenital: Urinary frequency and/or retention.

Causal Relationship Unknown

Other reactions, reported rarely for cyclobenzaprine under circumstances where a causal relationship could not be established or reported for other tricyclic drugs, are listed to serve as alerting information to physicians:

Body as a Whole: Chest pain; edema.
Cardiovascular: Hypertension; myocardial infarction; heart block; stroke.
Digestive: Paralytic ileus, tongue discoloration; stomatitis; parotid swelling.
Endocrine: Inappropriate ADH syndrome.
Hematic and Lymphatic: Purpura; bone marrow depression; leukopenia; eosinophilia; thrombocytopenia.
Metabolic, Nutritional and Immune: Elevation and lowering of blood sugar levels; weight gain or loss.
Musculoskeletal: Myalgia.
Nervous System and Psychiatric: Decreased or increased libido; abnormal gait; delusions; aggressive behavior; paranoia; peripheral neuropathy; Bell’s palsy; alteration in EEG patterns; extrapyramidal symptoms.
Respiratory: Dyspnea.
Skin: Photosensitization; alopecia.
Urogenital: Impaired urination; dilatation of urinary tract; impotence; testicular swelling; gynecomastia; breast enlargement; galactorrhea.

DRUG ABUSE AND DEPENDENCE

Pharmacologic similarities among the tricyclic drugs require that certain withdrawal symptoms be considered when AMRIX is administered, even though they have not been reported to occur with this drug. Abrupt cessation of treatment after prolonged administration rarely may produce nausea, headache, and malaise. These are not indicative of addiction.

OVERDOSAGE

Although rare, deaths may occur from overdosage with AMRIX. Multiple drug ingestion (including alcohol) is common in deliberate cyclobenzaprine overdose. As management of overdose is complex and changing, it is recommended that the physician contact a poison control center for current information on treatment. Signs and symptoms of toxicity may develop rapidly after cyclobenzaprine overdose; therefore, hospital monitoring is required as soon as possible. The acute oral LD50 of cyclobenzaprine is approximately 338 and 425 mg/kg in mice and rats, respectively.

Manifestations

The most common effects associated with cyclobenzaprine overdose are drowsiness and tachycardia. Less frequent manifestations include tremor, agitation, coma, ataxia, hypertension, slurred speech, confusion, dizziness, nausea, vomiting, and hallucinations. Rare but potentially critical manifestations of overdose are cardiac arrest, chest pain, cardiac dysrhythmias, severe hypotension, seizures, and neuroleptic malignant syndrome. Changes in the electrocardiogram, particularly in QRS axis or width, are clinically significant indicators of cyclobenzaprine toxicity. Other potential effects of overdosage include any of the symptoms listed under ADVERSE REACTIONS.

Management

General

As management of overdose is complex and changing, it is recommended that the physician contact a poison control center for current information on treatment.

In order to protect against the rare but potentially critical manifestations described above, obtain an ECG and immediately initiate cardiac monitoring. Protect the patient’s airway, establish an intravenous line, and initiate gastric decontamination. Observation with cardiac monitoring and observation for signs of CNS or respiratory depression, hypotension, cardiac dysrhythmias and/or conduction blocks, and seizures is necessary. If signs of toxicity occur at any time during this period, extended monitoring is required. Monitoring of plasma drug levels should not guide management of the patient. Dialysis is probably of no value because of low plasma concentrations of the drug.

Gastrointestinal Decontamination

All patients suspected of an overdose with AMRIX should receive gastrointestinal decontamination. This should include large volume gastric lavage followed by activated charcoal. If consciousness is impaired, the airway should be secured prior to lavage and emesis is contraindicated.

Cardiovascular

A maximal limb-lead QRS duration of 0.10 seconds may be the best indication of the severity of the overdose. Serum alkalinization, to a pH of 7.45 to 7.55, using intravenous sodium bicarbonate and hyperventilation (as needed), should be instituted for patients with dysrhythmias and/or QRS widening. A pH >7.60 or a pCO2 <20 mmHg is undesirable. Dysrhythmias unresponsive to sodium bicarbonate therapy/hyperventilation may respond to lidocaine, bretylium, or phenytoin. Type 1A and 1C antiarrhythmics are generally contraindicated (e.g., quinidine, disopyramide, and procainamide).

CNS

In patients with CNS depression, early intubation is advised because of the potential for abrupt deterioration. Seizures should be controlled with benzodiazepines or, if these are ineffective, other anticonvulsants (e.g., phenobarbital, phenytoin). Physostigmine is not recommended except to treat life-threatening symptoms that have been unresponsive to other therapies, and then only in close consultation with a poison control center.

Psychiatric Follow-up

Since overdosage is often deliberate, patients may attempt suicide by other means during the recovery phase. Psychiatric referral may be appropriate.

Pediatric Management

The principles of management of child and adult overdosage are similar. It is strongly recommended that the physician contact the local poison control center for specific pediatric treatment.

DOSAGE AND ADMINISTRATION

The recommended adult dose for most patients is one (1) AMRIX 15 mg capsule taken once daily. Some patients may require up to 30 mg/day, given as one (1) AMRIX 30 mg capsule taken once daily or as two (2) AMRIX 15 mg capsules taken once daily.

It is recommended that doses be taken at approximately the same time each day.

Use of AMRIX for periods longer than two or three weeks is not recommended (see INDICATIONS AND USAGE).

Dosage Considerations for Special Patient Populations: AMRIX should not be used in the elderly or in patients with impaired hepatic function. (see WARNINGS)

HOW SUPPLIED

AMRIX extended-release capsules are available in 15 mg strengths, packaged in bottles of 30 capsules. AMRIX 15 mg capsules (NDC 54868-6022-0) are orange/orange and are embossed in blue ink with “15 mg” on the body, and Cephalon “C” logo, “Cephalon”, and a dashed band on the cap.

Dispense in a tight, light-resistant container as defined in the USP/NF.
Store at 25°C (77°F); excursions permitted to 15 - 30°C (59 - 86°F); [see USP Controlled Room Temperature].

KEEP THIS AND ALL MEDICATION OUT OF THE REACH OF CHILDREN. IN CASE OF ACCIDENTAL OVERDOSE, SEEK PROFESSIONAL ASSISTANCE OR CONTACT A POISON CONTROL CENTER IMMEDIATELY.

Distributed by:
Cephalon, Inc.
Frazer, PA 19355

Manufactured by:
Eurand Inc.
Vandalia, Ohio 45377
AMRIX is a trademark of Cephalon, Inc. or its affiliates.

U.S. Patent No. 7,387,793

© 2004, 2006, 2007, 2008 Cephalon, Inc., or its affiliates. All rights reserved.

PI-40018-01
Revised December 2008

Relabeling and Repackaging by:
Physicians Total Care, Inc.
Tulsa, Oklahoma 74146

PACKAGE LABEL

Primary Display Panel for Amrix ER Capsules

15 mg